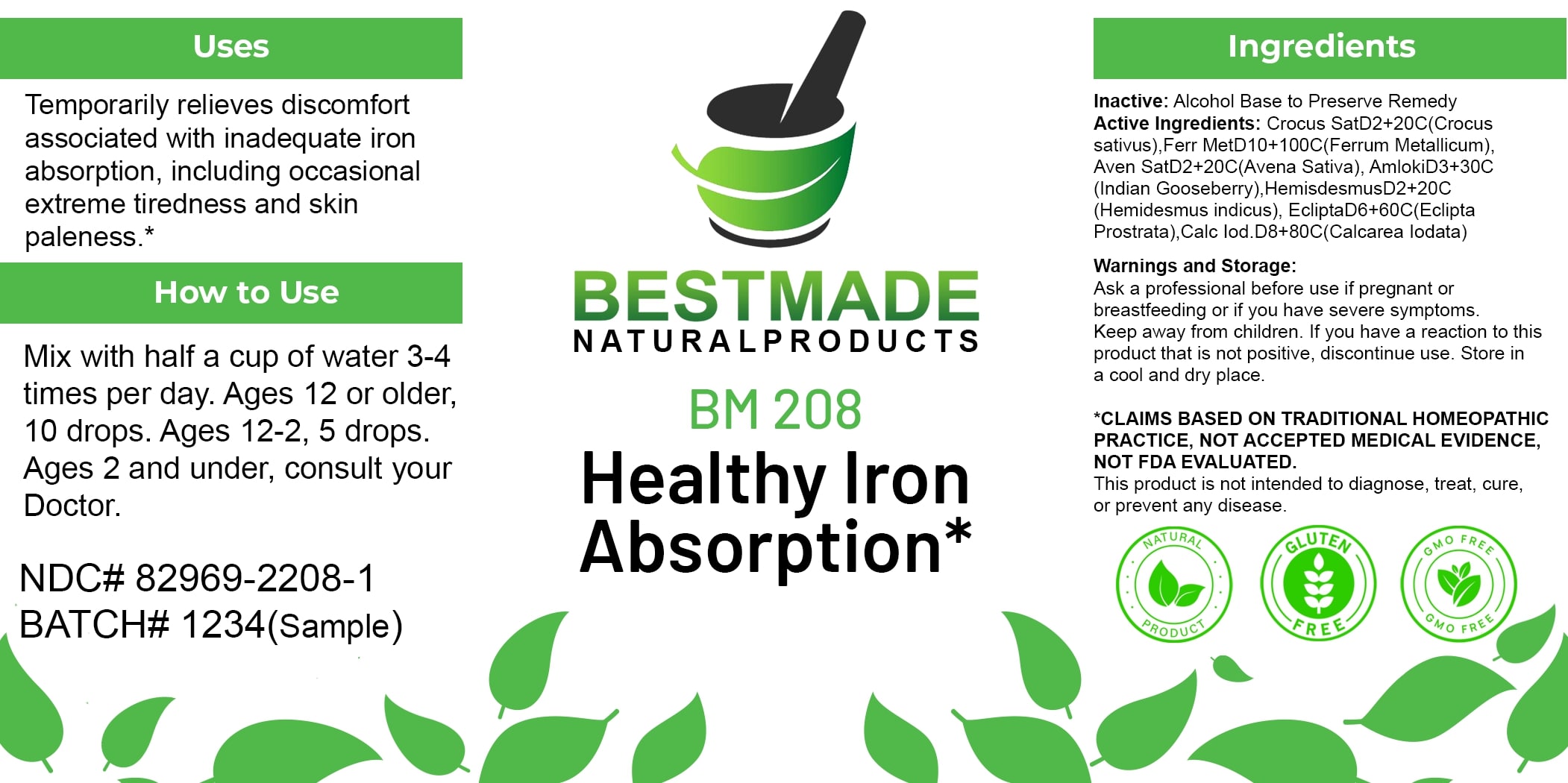 DRUG LABEL: Bestmade Natural Products BM208
NDC: 82969-2208 | Form: LIQUID
Manufacturer: Bestmade Natural Products
Category: homeopathic | Type: HUMAN OTC DRUG LABEL
Date: 20250228

ACTIVE INGREDIENTS: AVENA SATIVA FLOWERING TOP 30 [hp_C]/30 [hp_C]; IRON 30 [hp_C]/30 [hp_C]; PHYLLANTHUS EMBLICA FRUIT 30 [hp_C]/30 [hp_C]; CROCUS SATIVUS WHOLE 30 [hp_C]/30 [hp_C]; HEMIDESMUS INDICUS WHOLE 30 [hp_C]/30 [hp_C]; CALCIUM IODIDE 30 [hp_C]/30 [hp_C]; ECLIPTA PROSTRATA WHOLE 30 [hp_C]/30 [hp_C]
INACTIVE INGREDIENTS: ALCOHOL 30 [hp_C]/30 [hp_C]

BM208

DOSAGE AND ADMINISTRATION

How to Use

Mix with half a cup of water 3-4 times per day. Ages 12 or older, 10 drops. Ages 12-2, 5 drops. Ages 2 and under, consult your Doctor.

Uses

Temporarily relieves discomfort associated with inadequate iron absorption, including occasional extreme tiredness and skin paleness.*

*CLAIMS BASED ON TRADITIONAL HOMEOPATHIC PRACTICE, NOT ACCEPTED MEDICAL EVIDENCE. NOT FDA EVALUATED.

This product is not intended to diagnose, treat, cure, or prevent any disease.

INACTIVE INGREDIENT

Ingredients

Inactive: Alcohol Base to Preserve Remedy

ACTIVE INGREDIENT

Active Ingredients: Crocus SatD2+20C(Crocus sativus), Ferr MetD10+100C(Ferrum Metallicum), Aven SatD2+20C(Avena Sativa), AmikiD3+30C (Indian Gooseberry), HemidesmusD2+20C (Hemidesmus Indicus), EcliptaD6+60C(Eclipta Prostrata), Calc Iod D8+80C(Calcarea Iodata)

KEEP OUT OF REACH OF CHILDREN

Warnings and Storage:

Ask a professional before use if pregnant or breastfeeding or if you have severe symptoms. Keep away from children. If you have a reaction to this product that is not positive, discontinue use. Store in a cool and dry place.

Warnings and Storage:

Ask a professional before use if pregnant or breastfeeding or if you have severe symptoms. Keep away from children. If you have a reaction to this product that is not positive, discontinue use. Store in a cool and dry place.

*CLAIMS BASED ON TRADITIONAL HOMEOPATHIC PRACTICE, NOT ACCEPTED MEDICAL EVIDENCE. NOT FDA EVALUATED.

This product is not intended to diagnose, treat, cure, or prevent any disease.

Uses

Temporarily relieves discomfort associated with inadequate iron absorption, including occasional extreme tiredness and skin paleness.*

*CLAIMS BASED ON TRADITIONAL HOMEOPATHIC PRACTICE, NOT ACCEPTED MEDICAL EVIDENCE. NOT FDA EVALUATED.

This product is not intended to diagnose, treat, cure, or prevent any disease.

Entire package label